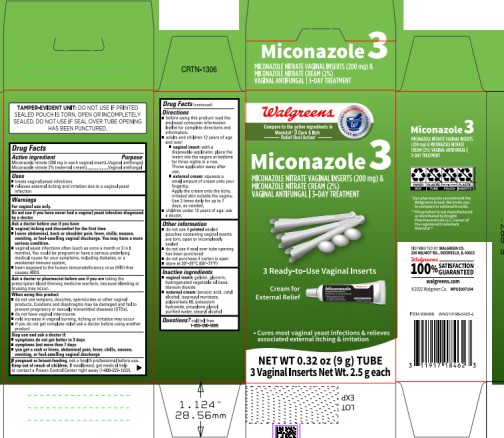 DRUG LABEL: Miconazole 3
NDC: 0363-5203 | Form: KIT | Route: VAGINAL
Manufacturer: WALGREEN COMPANY
Category: otc | Type: HUMAN OTC DRUG LABEL
Date: 20260123

ACTIVE INGREDIENTS: MICONAZOLE NITRATE 200 mg/1 1; MICONAZOLE NITRATE 20 mg/1 g
INACTIVE INGREDIENTS: GLYCERIN; TITANIUM DIOXIDE; GELATIN; BENZOIC ACID; CETYL ALCOHOL; ISOPROPYL MYRISTATE; POLYSORBATE 60; POTASSIUM HYDROXIDE; PROPYLENE GLYCOL; WATER; STEARYL ALCOHOL

Miconazole 3 Combination Pack

Drug Facts

Active ingredients

Miconazole nitrate (200 mg in each vaginal insert)

Miconazole nitrate 2% (external cream)

Purpose

Vaginal antifungal

Vaginal antifungal

Uses

- treats vaginal yeast infections
- relieves external itching and irritation due to a vaginal yeast infection

Warnings

For vaginal use only

Do not use

if you have never had a vaginal yeast infection diagnosed by a doctor.

Ask a doctor before use if you have

- vaginal itching and discomfort for the first time
- lower abdominal, back or shoulder pain, fever, chills, nausea, vomiting, or foul-smelling vaginal discharge. You may have a more serious condition.
- vaginal yeast infections often (such as once a month or 3 in 6 months). You could be pregnant or have a serious underlying medical cause for your symptoms, including diabetes, or a weakened immune system.
- been exposed to the human immunodeficiency virus (HIV) that causes AIDS

Ask a doctor or pharmacist before use if you are

taking the prescription blood thinning medicine warfarin, because bleeding or bruising may occur

When using this product

- do not use tampons, douches, spermicides or other vaginal products. Condoms and diaphragms may be damaged and fail to prevent pregnancy or sexually transmitted diseases (STDs)
- do not have vaginal intercourse
- mild increase in vaginal burning, itching or irritation may occur
- if you do not get complete relief ask a doctor before using another product

Stop use and ask a doctor if:

- symptoms do not get better in 3 days
- symptoms last more than 7 days
- you get a rash or hives, abdominal pain, fever, chills, nausea, vomiting, or foul-smelling vaginal discharge.

If pregnant or breast-feeding,

ask a health professional before use.

Keep out of reach of children.

If swallowed, get medical help or contact a Poison Control Center right away (1-800-222-1222).

Directions

- before using this product read the enclosed consumer information leaflet for complete directions and information
- adults and children 12 years of age and over:
  - vaginal insert: with a disposable applicator, place the insert into the vagina at bedtime for three nights in a row. Throw applicator away after use.
  - external cream: squeeze a small amount of cream onto your fingertip. Apply the cream onto the itchy, irritated skin outside the vagina. Use 2 times daily for up to 7 days, as needed.
- children under 12 years of age: ask a doctor.

Other Information

- do not use if printed sealed pouches containing vaginal inserts are torn, open or incompletely sealed
- do not use if seal over tube opening has been punctured
- do not purchase if carton is open
- store at 20°-25°C (68°-77°F)

Inactive ingredients

vaginal insert: gelatin, glycerin, hydrogenated vegetable oil base, titanium dioxide

external cream: benzoic acid, cetyl alcohol, isopropyl myristate, polysorbate 60, potassium hydroxide, propylene glycol, purified water, stearyl alcohol.

Questions?

call toll-free 1-855-590-5695

PRINCIPAL DISPLAY PANEL

- Kit Carton

Miconazole 3

Miconazole Nitrate Vaginal Inserts (200 mg) &

Miconazole Nitrate Cream (2%)

Vaginal Antifungal | 3-Day Treatment

3 Ready-to-Use Vaginal Inserts

Cream for External Relief

Net Wt. 0.32 oz (9 g) TUBE

3 Vaginal Inserts Net Wt. 2.5 g each